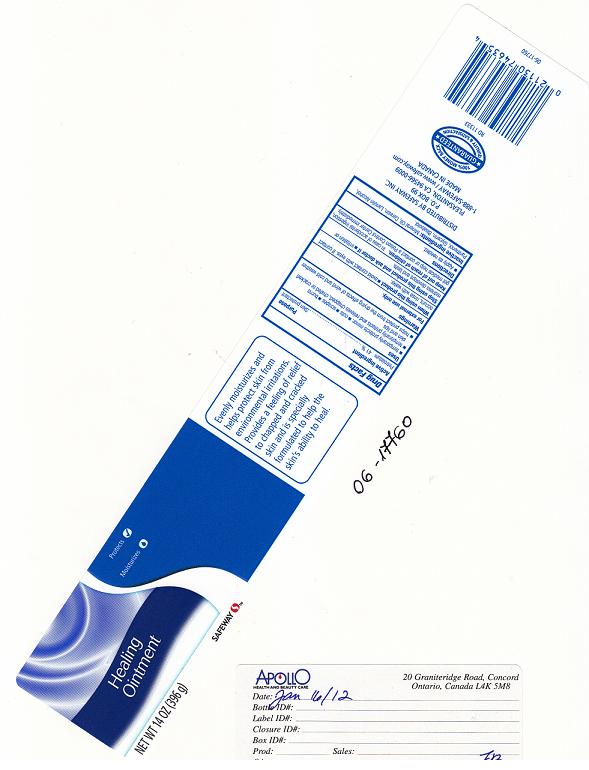 DRUG LABEL: SAFEWAY
NDC: 21130-330 | Form: JELLY
Manufacturer: SAFEWAY INC.
Category: otc | Type: HUMAN OTC DRUG LABEL
Date: 20111215

ACTIVE INGREDIENTS: PETROLATUM 41.0 g/100 g
INACTIVE INGREDIENTS: MINERAL OIL; CERESIN; LANOLIN ALCOHOLS; PANTHENOL; GLYCERIN; .ALPHA.-BISABOLOL, (+/-)-

DRUG FACTS

ACTIVE INGREDIENT

PETROLATUM 41%

PURPOSE

SKIN PROTECTANT

USES

TEMPORARILY PROTECTS MINOR: CUTS, SCRAPES, BURNS.

TEMPORARILY PROTECTS AND RELIEVES CHAPPED, CHAFED OR CRACKED SKIN AND LIPS.

HELPS PROTECT FROM THE DRYING EFFECTS OF WIND AND COLD WEATHER.

WARNINGS

FOR EXTERNAL USE ONLY.

WHEN USING THIS PRODUCT

AVOID CONTACT WITH EYES. IF CONTACT OCCURS, RINSE WITH WATER.

STOP USING THIS PRODUCT AND ASK DOCTOR IF

IRRITATION OR REDNESS DEVELOPS AND LASTS.

KEEP OUT OF REACH OF CHILDREN

IN CASE OF ACCIDENTAL INGESTION, GET MEDICAL HELP OR CONTACT A POISON CONTROL CENTER IMMEDIATELY.

DIRECTIONS

APPLY AS NEEDED.

INACTIVE INGREDIENTS:

MINERAL OIL, CERESIN, LANOLIN ALCOHOL, PANTHENOL, GLYCERIN, BISABOLOL.